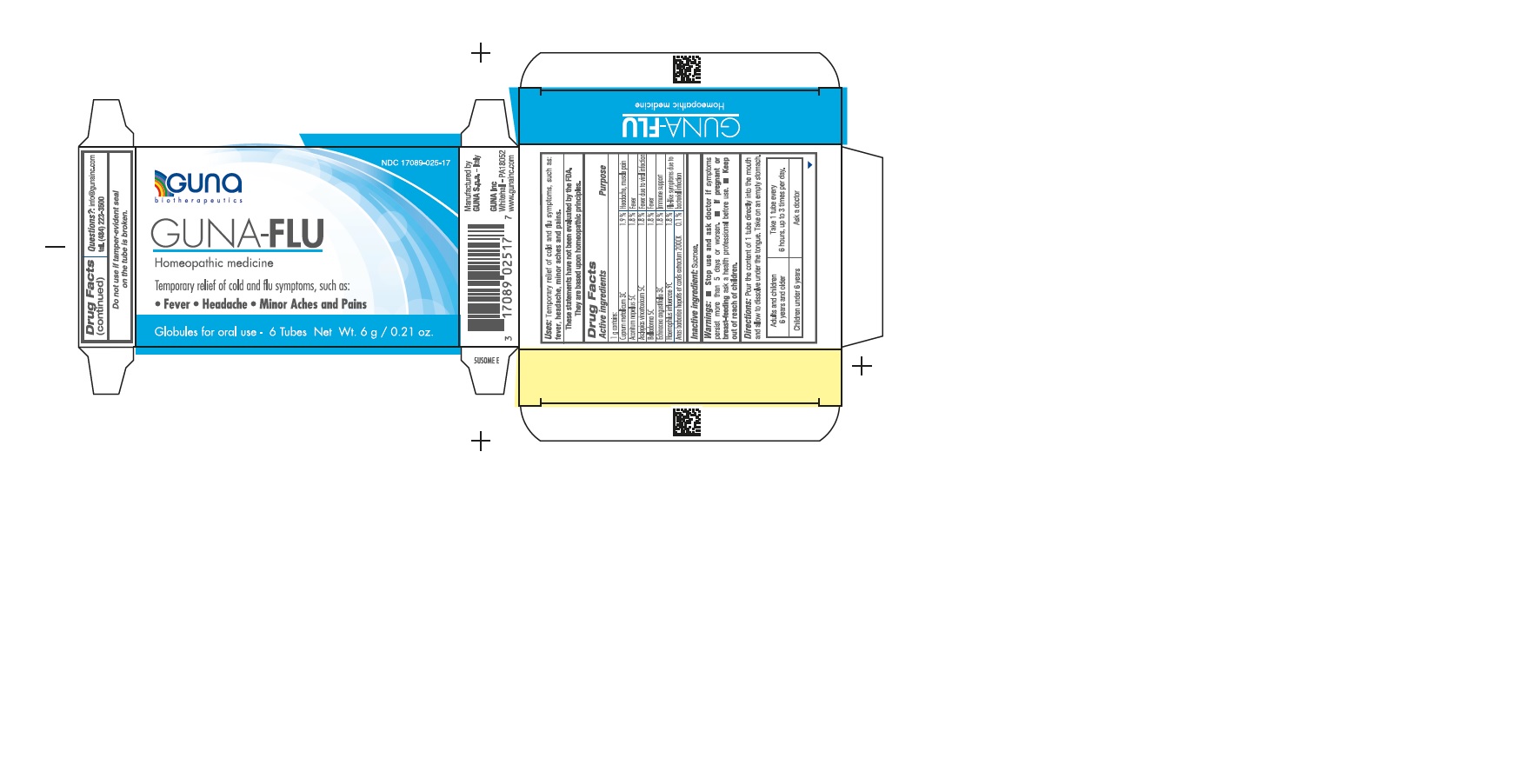 DRUG LABEL: GUNA-FLU
NDC: 17089-025 | Form: PELLET
Manufacturer: Guna spa
Category: homeopathic | Type: HUMAN OTC DRUG LABEL
Date: 20221114

ACTIVE INGREDIENTS: ACONITUM NAPELLUS 5 [hp_C]/1 g; CAIRINA MOSCHATA HEART/LIVER AUTOLYSATE 7 [hp_C]/1 g; ASCLEPIAS CURASSAVICA 5 [hp_C]/1 g; ATROPA BELLADONNA 5 [hp_C]/1 g; COPPER 3 [hp_C]/1 g; ECHINACEA ANGUSTIFOLIA 3 [hp_C]/1 g; HAEMOPHILUS INFLUENZAE TYPE B 9 [hp_C]/1 g
INACTIVE INGREDIENTS: SUCROSE 0.8 g/1 g

GUNA-FLU

ACTIVE INGREDIENTS/PURPOSE

ACONITUM NAPELLUS 5C FEVER
ANAS BARBARIAE 200CK FLU-LIKE SYMPTOMS DUE TO BACTERIAL INFECTIONS
ASCLEPIAS VINCETOXICUM 5C FEVER DUE TO VIRAL INFECTIONS
BELLADONNA 5C FEVER
CUPRUM METALLICUM 3C HEADACHE, MUSCLE PAIN
ECHINACEA ANGUSTIFOLIA 3C IMMUNE SUPPORT
HAEMOPHILUS INFLUENZAE 9C FLU-LIKE SYMPTOMS DUE TO BACTERIAL INFECTIONS

USES

- Uses: Temporary relief of cold and flu symptoms, such as: fever, headache, minor aches and pains.

WARNINGS

- Stop use and ask doctor if symptoms persist more than 5 days or worsen.

PREGNANCY

If pregnant or breast-feeding ask a health professional before use.

WARNINGS

- Stop use and ask doctor if symptoms persist more than 5 days or worsen.
- If pregnant or breast-feeding ask a health professional before use.
- Keep out of reach of children.

DIRECTIONS

Take on an empty stomach.
Adults and children 12 years and older Take 1 tube contents to be dissolved in the mouth, every 6 hours, up to 3 times per day.
Children between 12 years and 6 years of age. Take 1 tube contents to be dissolved into a little water, every 6 hours, up to 3 times per day.
Children under 6 years Consult a physician.

QUESTIONS

Questions?: info@gunainc.com
tel. (484) 223-3500

DOSAGE AND ADMINISTRATION

- Adults and children 6 years and older: take 1 tube every 6 hours, up to 3 times per day.
- Children under 6 years: Ask a doctor.

INDICATIONS AND USAGE

- Directions: pour the content of 1 tube directly into the mouth and allow to dissolve under the tongue. Take on an empty stomach.

- Inactive Ingredient: Sucrose.

- keep out of reach of children.

- Stop use and ask doctor if symptoms persist more than 5 days or worsen.
- If pregnant or breast-feeding ask a health professional before use.
- Keep out of reach of children.